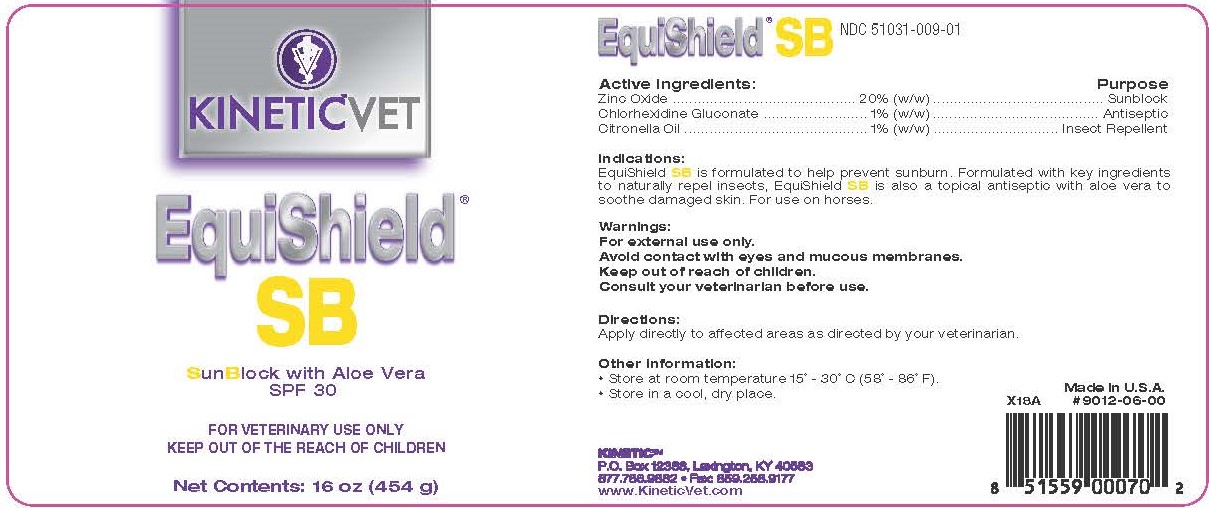 DRUG LABEL: EquiShield SB
NDC: 51031-009 | Form: CREAM
Manufacturer: Kinetic Technologies, LLC
Category: animal | Type: OTC ANIMAL DRUG LABEL
Date: 20231127

ACTIVE INGREDIENTS: ZINC OXIDE 20 g/100 g; CHLORHEXIDINE GLUCONATE 1 g/100 g; CITRONELLA OIL 1 g/100 g

EquiShield SB

Active Ingredients:

Zinc Oxide.................................... 20% (w/w)..................Sunblock

Chlorhexidine Gluconate................... 1% (w/w).................Antiseptic

Citronella Oil................................... 1% (w/w).........Insect Repellent

Indications:

EquiShield SB is formulated to help prevent sunburn. Formulated with key ingredients to naturally repel insects, EquiShield SB is also a topical antiseptic with aloe vera to soothe damaged skin. For use on horses.

Warnings:

For external use only.

Avoid contact with eyes and mucous membranes.

Keep out of reach of children.

Consult your veterinarian before use.

Directions:

Apply directly to affected areas as directed by your veterinarian.

Other Information:

• Store at room temperature 15° - 30°C (58° - 86°F)

• Store in a cool, dry place

Made in U.S.A.

#9012-06-00

KINETIC™

P.O. Box 12388, Lexington, KY 40583

877.786.9882 • Fax: 859.258.9177

www.KineticVet.com

KINETIC™VET

EquiShield® SB

SunBlock with Aloe Vera

SPF 30

FOR VETERINARY USE ONLY

KEEP OUT OF THE REACH OF CHILDREN

Net Contents: 16 oz (454 g)